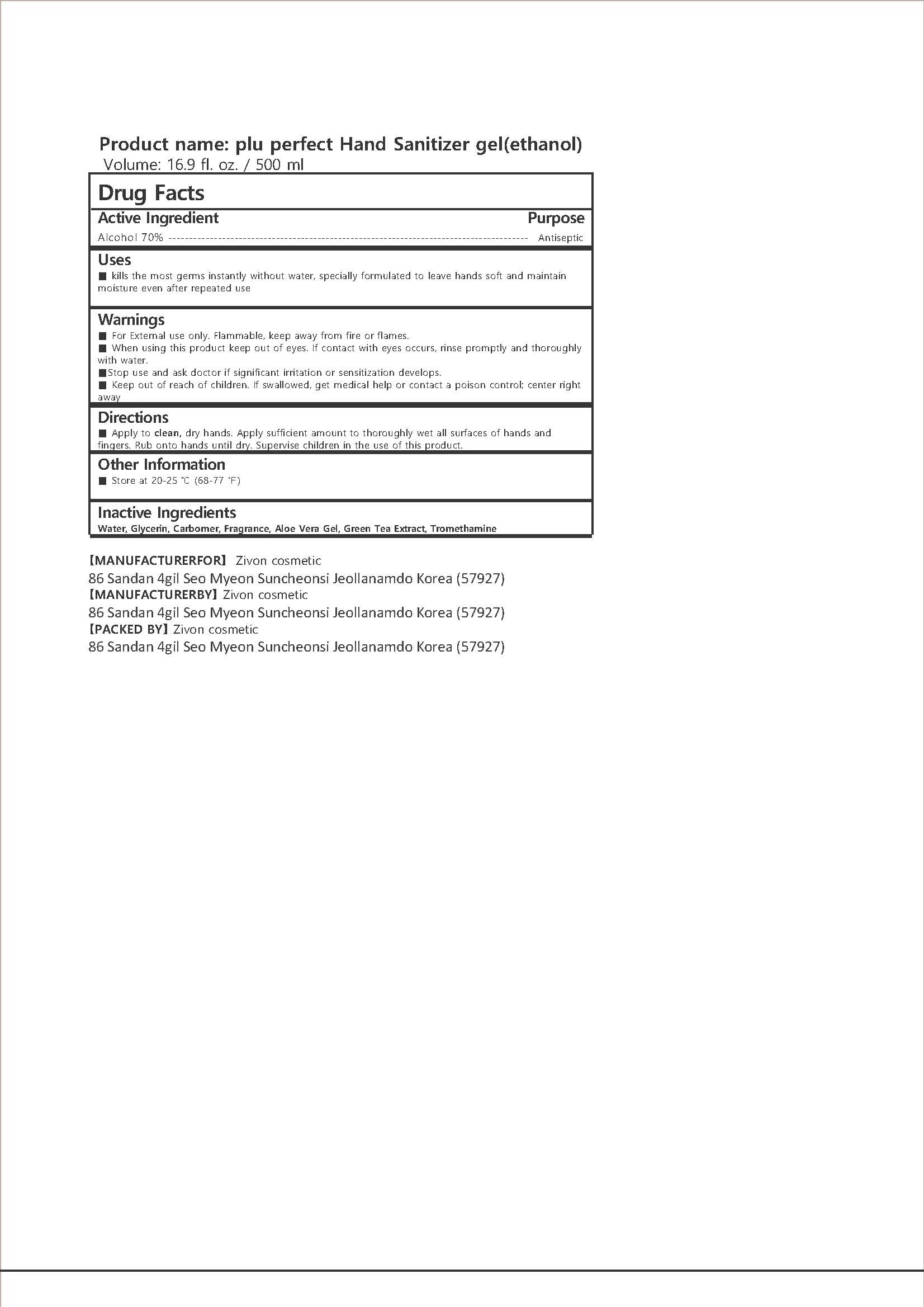 DRUG LABEL: Plu Perfect Hand Sanitizer Gel
NDC: 71503-117 | Form: GEL
Manufacturer: Zivon Cosmetic Co., Ltd.
Category: otc | Type: HUMAN OTC DRUG LABEL
Date: 20200602

ACTIVE INGREDIENTS: ALCOHOL 350 mL/500 mL
INACTIVE INGREDIENTS: TROLAMINE; ALOE VERA WHOLE; WATER; GLYCERIN; CARBOMER HOMOPOLYMER, UNSPECIFIED TYPE; GREEN TEA LEAF

Drug Facts

ACTIVE INGREDIENT

Alcohol

INACTIVE INGREDIENT

Water, Glycerin, Carbomer, Fragrance, Aloe Vera Gel, Green Tea Extract, Tromethamine

PURPOSE

Antiseptic

KEEP OUT OF REACH OF THE CHILDREN

INDICATIONS AND USAGE

For the external use only

WARNINGS

For external use only.

Flammable, keep away from fire or flame.

When using this product keep out of eyes. If contact with eyes occurs, rinse promptly and thoroughly with water.

Stop use and ask a doctor if significant irritation or sensitization develops.

Keep out of reach of children. If swallowed, get medical help or contact a Poison Control Center right away.

DOSAGE AND ADMINISTRATION

Apply to clean, dry hands.

Apply sufficient amount to thoroughly wet all surfaces of hands and fingers.

Rub onto hands until dry.

Supervise children in the use of this product.